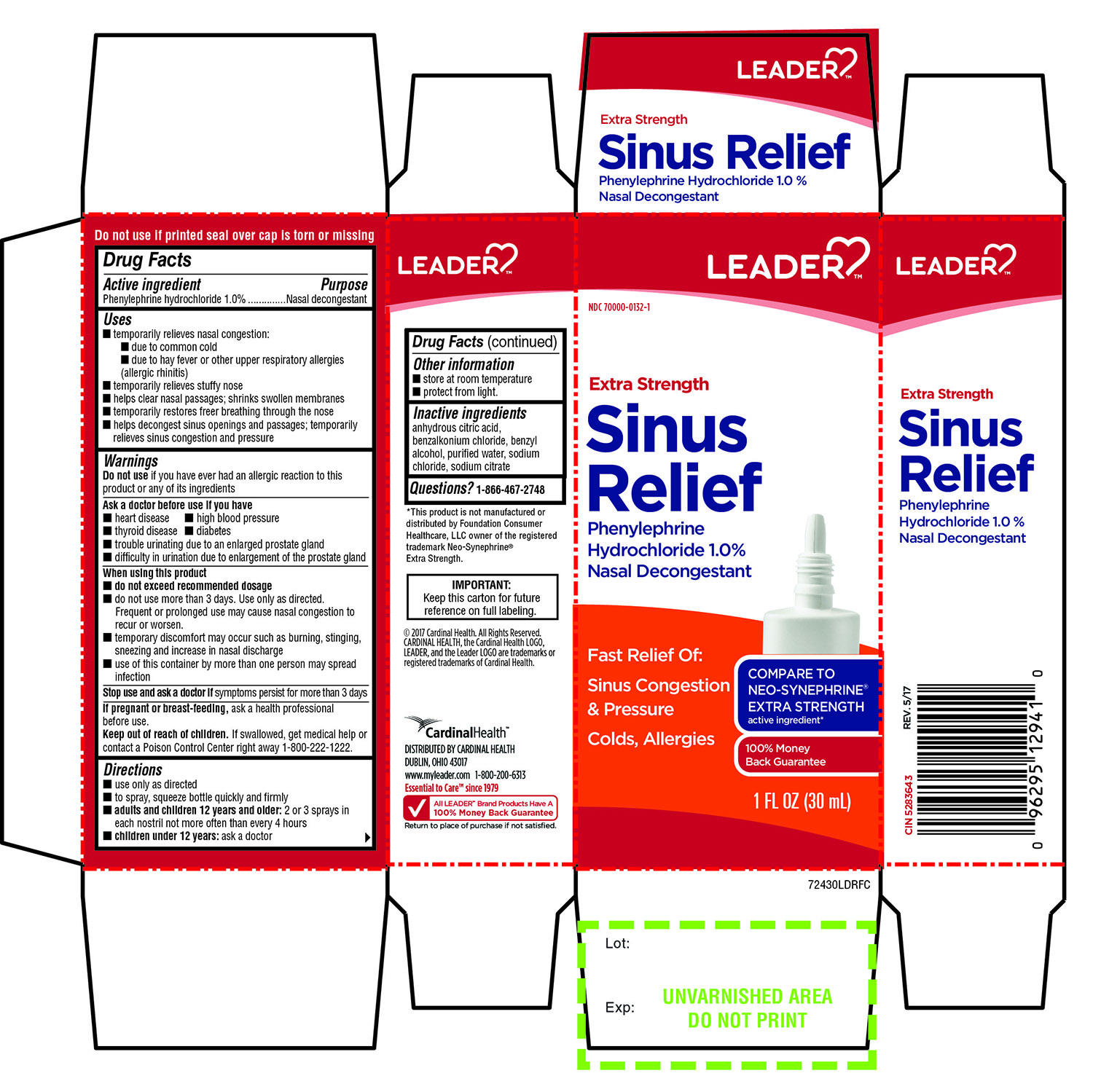 DRUG LABEL: Extra Strength Sinus Relief Nasal Decongestant
NDC: 70000-0132 | Form: SPRAY
Manufacturer: CARDINAL HEALTH
Category: otc | Type: HUMAN OTC DRUG LABEL
Date: 20251014

ACTIVE INGREDIENTS: PHENYLEPHRINE HYDROCHLORIDE 1 g/100 mL
INACTIVE INGREDIENTS: ANHYDROUS CITRIC ACID; BENZALKONIUM CHLORIDE; BENZYL ALCOHOL; WATER; SODIUM CHLORIDE; SODIUM CITRATE, UNSPECIFIED FORM

LEADER Extra Strength Sinus Relief Phenylephrine Hydrochloride 1.0% Nasal Decongestant 1 FL OZ

Active ingredients

Phenylephrine Hydrochloride 1.0 %

Purpose

Nasal decongestant

Uses

- temporarily relieves nasal congestion:
- due to common cold
- due to hay fever or other upper respiratory allergies (allergic rhinitis)
- temporarily relieves stuffy nose.
- helps clear nasal passages; shrinks swollen membranes
- temporarily restores freer breathing through the nose
- helps decongest sinus openings and passages; temporarily relieves sinus congestion and pressure

Warnings

Do Not Use

If you have ever had an allergic reaction to this product or any of its ingredients

Ask a doctor before use if you have

- heart disease
- high blood pressure
- thyroid disease
- diabetes
- trouble urinating due to an enlarged prostate gland
- difficulty in urination due to enlargement of the prostate gland

When using this product

- do not exceed recommended dosage
- do not use for more than 3 days. Use only as directed.

Frequent or prolonged use may cause nasal congestion to recur or worsen

- temporary discomfort may occur such as burning, stinging, sneezing and increase in nasal discharge
- use of this container by more than one person may spread infection

Stop use and ask a doctor if

symptoms persist for more than 3 days.

If pregnant or breast-feeding

ask a health professional before use.

Keep out of reach of children.

If swallowed, get medical help or contact a Poison Control Center right away 1-800-222-1222

Directions

- Use only as directed
- to spray, squeeze bottle quickly and firmly
- adults and children 12 years older:2 or 3 sprays in each nostril not more often than every 4 hours.
- children under 12 years :ask a doctor

Other information

- store at room temperature
- Protect from light.

Inactive ingredients

anhydrous citric acid, benzalkonium chloride, benzyl alcohol, purified water, sodium chloride, sodium citrate

Questions

1-866-467-2748

Principal Display

LEADER

NDC 70000-0132-1

COMPARE TO NEO-SYNEPHRINE®EXTRA STRENGTH active ingredient

Extra Strength

Sinus Relief

Phenylephrine hydrochloride 1.0 %

Nasal Decongestant

Fast Relief Of:

Sinus Congestion & Pressure

- Colds, Allergies

1 FL OZ (30 mL)

* This product is not manufactured or distributed by Foundation Consumer Healthcare LLC owner of the registered trademark Neo-Synephrine®Extra Strength.

IMPORTANT: Keep this carton for future reference on full labeling.

Do not use if printed seal over cap is torn or missing

©2017 Cardinal Health, All Rights Reserved , CARDINAL HEALTH ,the Cardinal Health LOGO, LEADER, and the Leader LOGO are trademarks or registered trademarks of Cardinal Health.

Cardinal Health™

DISTRIBUTED BY CARDINAL HEALTH

DUBLIN, OHIO 43017

www.myleader.com

1-800-200-6313

Essential to care™ since 1979

* This product is not manufactured or distributed by Foundation Consumer Healthcare LLC owner of the registered trademark Neo-Synephrine®Extra Strength.